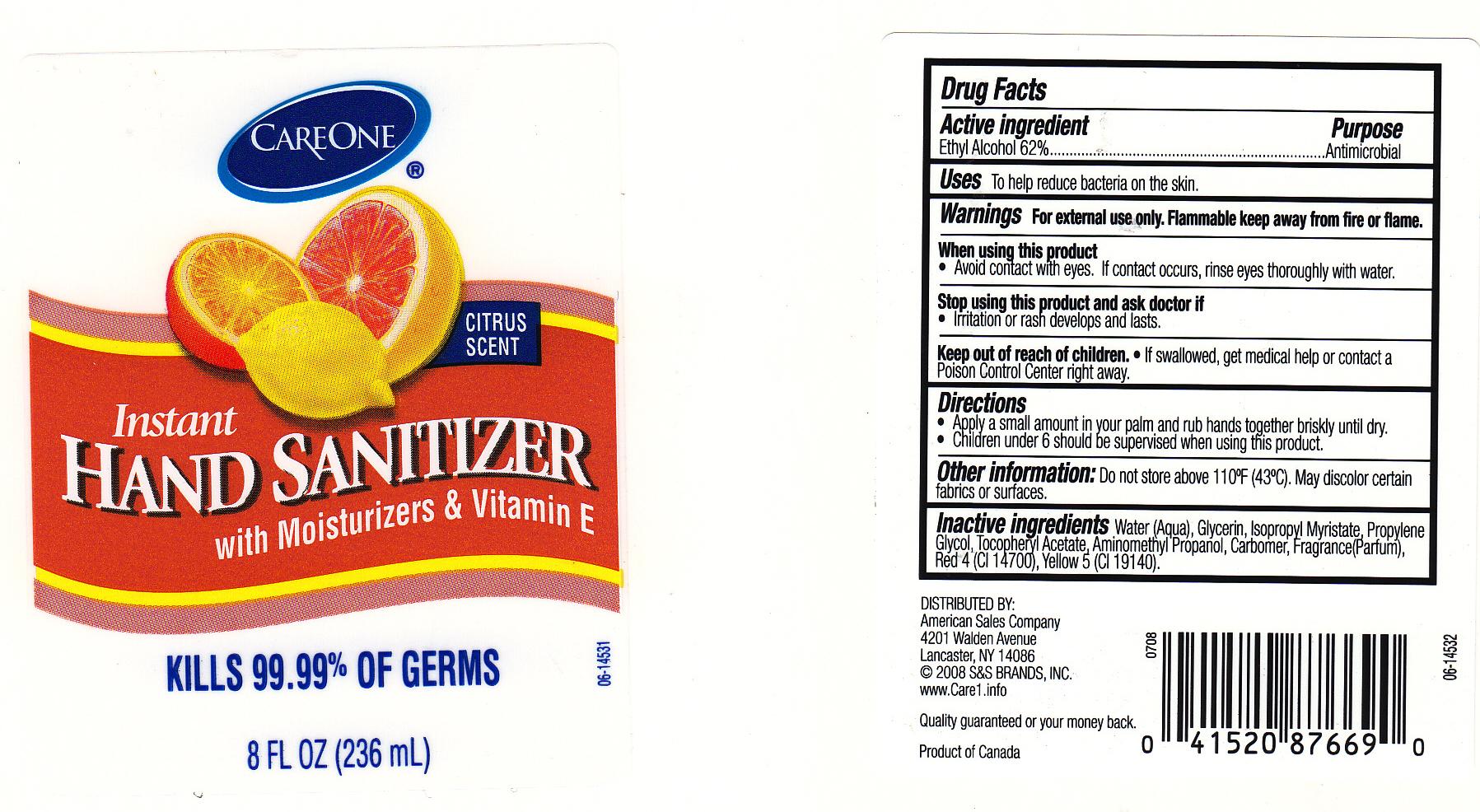 DRUG LABEL: INSTANT HAND SANITIZER
NDC: 41520-230 | Form: GEL
Manufacturer: AMERICAN SALES COMPANY
Category: otc | Type: HUMAN OTC DRUG LABEL
Date: 20111005

ACTIVE INGREDIENTS: ALCOHOL 62 mL/100 mL
INACTIVE INGREDIENTS: WATER; GLYCERIN; ISOPROPYL MYRISTATE; PROPYLENE GLYCOL; .ALPHA.-TOCOPHEROL ACETATE, D-; AMINOMETHYLPROPANOL; CARBOMER 934; FD&C RED NO. 4; FD&C YELLOW NO. 5

DRUG FACTS

ACTIVE INGREDIENT

ETHYL ALCOHOL 62%

PURPOSE

ANTIMICROBIAL

USES

TO HELP REDUCE BACTERIA ON THE SKIN.

WARNINGS

FOR EXTERNAL USE ONLY. FLAMMABLE KEEP AWAY FROM FIRE OR FLAME.

WHEN USING THIS PRODUCT

AVOID CONTACT WITH EYES. IF CONTACT OCCURS, RINSE EYES THOROUGHLY WITH WATER.

STOP USING THIS PRODUCT AND ASK DOCTOR IF

IRRITATION OR RASH DEVELOPS AND LASTS.

KEEP OUT OF REACH OF CHILDREN

IF SWALLOWED, GET MEDICAL HELP OR CONTACT A POISON CONTROL CENTER RIGHT AWAY.

DIRECTIONS

- APPLY A SMALL AMOUNT IN YOUR PALM AND RUB HANDS TOGETHER BRISKLY UNTIL DRY.
- CHILDREN UNDER 6 SHOULD BE SUPERVISED WHEN USING THIS PRODUCT.

OTHER INFORMATION

DO NOT STORE ABOVE 110OC (43 OC). MAY DISCOLOR CERTAIN FABRICS OR SURFACES.

INACTIVE INGREDIENTS

WATER, GLYCERIN, ISOPROPYL MYRISTATE, PROPYLENE GLYCOL, TOCOPHERYL ACETATE, AMINOMETHYL PROPANOL, CARBOMER, FRAGRANCE, RED 4 (CI 14700), YELLOW (CI 19140).